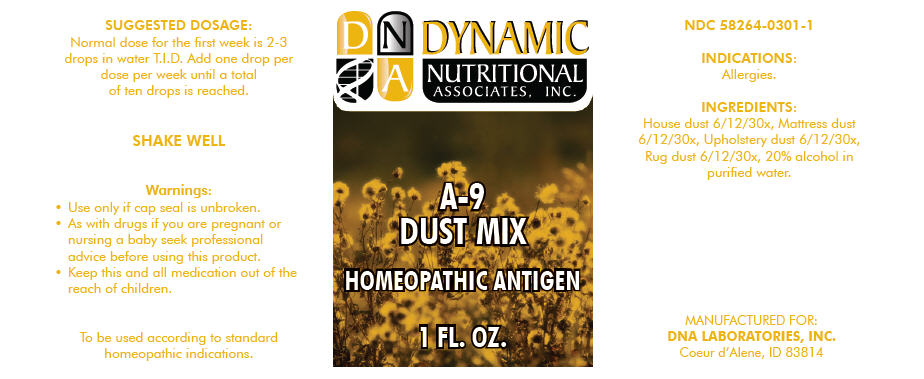 DRUG LABEL: A-9
NDC: 58264-0301 | Form: SOLUTION
Manufacturer: DNA Labs, Inc.
Category: homeopathic | Type: HUMAN OTC DRUG LABEL
Date: 20250109

ACTIVE INGREDIENTS: HOUSE DUST 30 [hp_X]/1 mL
INACTIVE INGREDIENTS: ALCOHOL; WATER

A-9

NDC 58264-0301-1

INDICATIONS

PURPOSE

Allergies.

INGREDIENTS

INACTIVE INGREDIENT

House dust 6/12/30x, Mattress dust 6/12/30x, Upholstery dust 6/12/30x, Rug dust 6/12/30x, 20% alcohol in purified water.

SUGGESTED DOSAGE

Normal dose for the first week is 2-3 drops in water T.I.D. Add one drop per dose per week until a total of ten drops is reached.

SHAKE WELL

Warnings

- Use only if cap seal is unbroken.

PREGNANCY OR BREAST FEEDING

- As with drugs if you are pregnant or nursing a baby seek professional advice before using this product.

KEEP OUT OF REACH OF CHILDREN

- Keep this and all medication out of the reach of children.

To be used according to standard homeopathic indications.

PRINCIPAL DISPLAY PANEL - 1 FL. OZ. Bottle Label

DYNAMIC
NUTRITIONAL
ASSOCIATES, INC.

A-9
DUST MIX

HOMEOPATHIC ANTIGEN

1 FL. OZ.